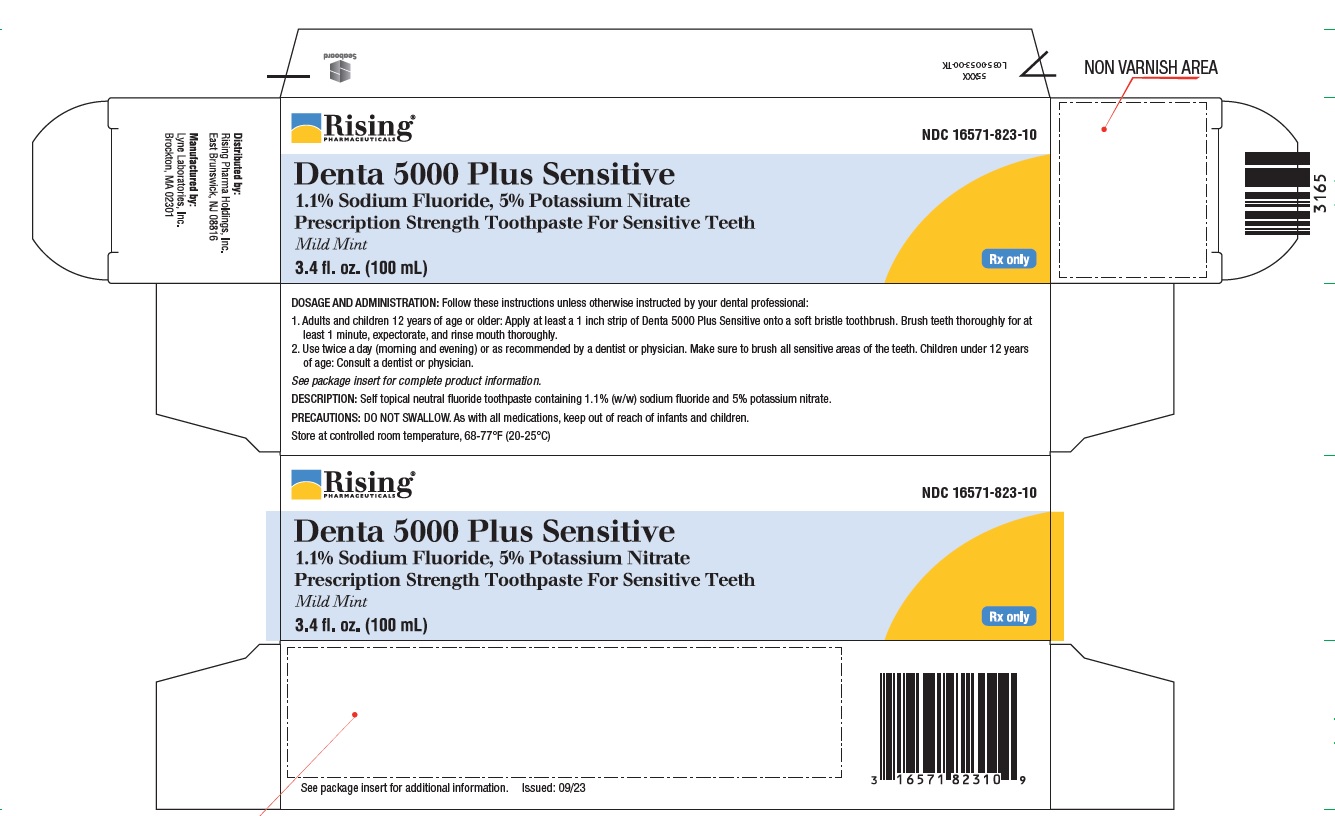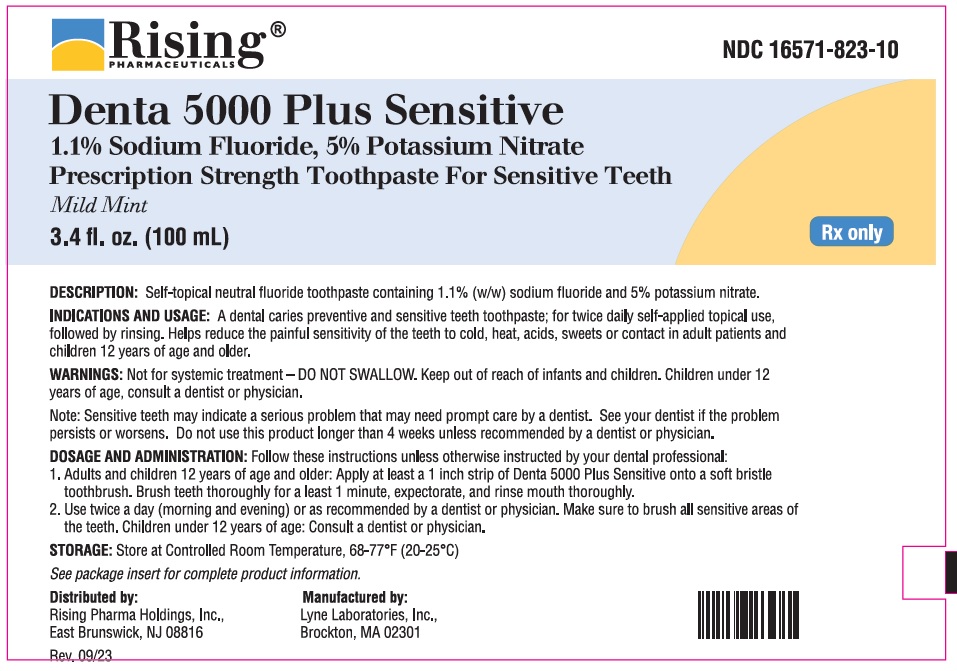 DRUG LABEL: Denta 5000 Plus Sensitive
NDC: 16571-823 | Form: GEL, DENTIFRICE
Manufacturer: Rising Pharma Holdings, Inc.
Category: prescription | Type: HUMAN PRESCRIPTION DRUG LABEL
Date: 20231109

ACTIVE INGREDIENTS: SODIUM FLUORIDE 5.8 mg/1 mL; POTASSIUM NITRATE 57.5 mg/1 mL
INACTIVE INGREDIENTS: FD&C BLUE NO. 1; HYDRATED SILICA; POLYETHYLENE GLYCOL 600; SORBITOL; CARBOXYMETHYLCELLULOSE SODIUM, UNSPECIFIED; SODIUM BENZOATE; SUCRALOSE; TITANIUM DIOXIDE; SODIUM HYDROXIDE; SODIUM LAURYL SULFATE; D&C YELLOW NO. 10; WATER

Denta 5000 Plus Sensitive
1.1% Sodium Fluoride, 5% Potassium Nitrate
Prescription Strength Toothpaste For Sensitive Teeth
Mild Mint

DENTA 5000 PLUS SENSITIVE BRAND OF 1.1% SODIUM FLUORIDE, 5% POTASSIUM NITRATE PRESCRIPTION STRENGTH TOOTHPASTE FOR SENSITIVE TEETH

Rx Only

Description:

Self-topical neutral fluoride toothpaste containing 1.1% (w/w) sodium fluoride and 5% potassium nitrate.

Active Ingredients:

Potassium Nitrate 5%, Sodium Fluoride 1.1% (w/w)

Inactive Ingredients:

Sorbitol, Hydrated Silica, PEG 600, Sodium Carboxymethylcellulose, Flavor, Sodium Lauryl Sulfate, Sodium Benzoate, Sucralose, Titanium Dioxide, Sodium Hydroxide, FD&C Blue #1, D&C Yellow #10, Purified Water.

CLINICAL PHARMACOLOGY:

Frequent topical applications to the teeth with preparations having a relatively high fluoride content increase tooth resistance to acid dissolution and enhance penetration of the fluoride ion into tooth enamel.

INDICATIONS AND USAGE:

A dental caries preventive and sensitive teeth toothpaste; for twice daily self-applied topical use, followed by rinsing. Helps reduce the painful sensitivity of the teeth to cold, heat, acids, sweets or contact in adult patients and children 12 years of age and older. It is well established that 1.1% sodium fluoride is safe and extraordinarily effective as a caries preventive when applied frequently with mouthpiece applicators.^1-4 Denta 5000 Plus Sensitive 1.1% sodium fluoride toothpaste with 5% potassium nitrate in a squeeze tube is easily applied onto a toothbrush. This prescription toothpaste should be used twice daily in place of your regular toothpaste unless otherwise instructed by your dental professional. May be used in areas where drinking water is fluoridated since topical fluoride cannot produce fluorosis. (See WARNINGS for exception.)

CONTRAINDICATIONS:

Do not use in pediatric patients under age 12 years unless recommended by a dentist or physician.

WARNINGS:

Not for systemic treatment - DO NOT SWALLOW. Keep out of reach of infants and children. Children under 12 years of age, consult a dentist or physician.

Note: Sensitive teeth may indicate a serious problem that may need prompt care by a dentist. See your dentist if the problem persists or worsens. Do not use this product longer than 4 weeks unless recommended by a dentist or physician.

PRECAUTIONS:

General:

Not for systemic treatment. DO NOT SWALLOW.

Carcinogenesis, Mutagenesis, Impairment of Fertility:

In a study conducted in rodents, no carcinogenesis was found in male and female mice and female rats treated with fluoride at dose levels ranging from 4.1 to 9.1 mg/kg of body weight. Equivocal evidence of carcinogenesis was reported in male rats treated with 2.5 and 4.1 mg/kg of body weight. In a second study, no carcinogenesis was observed in rats, males or females, treated with fluoride up to 11.3 mg/kg of body weight. Epidemiological data provide no credible evidence for an association between fluoride, either naturally occurring or added to drinking water, and risk of human cancer. Fluoride ion is not mutagenic in standard bacterial systems. It has been shown that fluoride ion has potential to induce chromosome aberrations in cultured human and rodent cells at doses much higher than those to which humans are exposed. In vivo data are conflicting. Some studies report chromosome damage in rodents, while other studies using similar protocols report negative results. Potential adverse reproductive effects of fluoride exposure in humans have not been adequately evaluated. Adverse effects on reproduction were reported for rats, mice, fox, and cattle exposed to 100 ppm or greater concentrations of fluoride in their diet or drinking water. Other studies conducted in rats demonstrated that lower concentrations of fluoride (5 mg/kg of body weight) did not result in impaired fertility and reproductive capabilities.

Pregnancy: Teratogenic Effects:

Pregnancy Category B.

It has been shown that fluoride crosses the placenta of rats, but only 0.01% of the amount administered is incorporated in fetal tissue. Animal studies (rats, mice, rabbits) have shown that fluoride is not a teratogen. Maternal exposure to 12.2 mg fluoride/kg of body weight (rats) or 13.1 mg/kg of body weight (rabbits) did not affect the litter size or fetal weight and did not increase the frequency of skeletal or visceral malformations. There are no adequate and well-controlled studies in pregnant women. However, epidemiological studies conducted in areas with high levels of naturally fluoridated water showed no increase in birth defects. Heavy exposure to fluoride during in utero development may result in skeletal fluorosis which becomes evident in childhood.

Nursing Mothers:

It is not known if fluoride is excreted in human milk. However, many drugs are excreted in milk, and caution should be exercised when products containing fluoride are administered to a nursing woman. Reduced milk production was reported in farm-raised fox when the animals were fed a diet containing a high concentration of fluoride (98-137 mg/kg of body weight). No adverse effects on parturition, lactation, or offspring were seen in rats administered fluoride up to 5 mg/kg of body weight.

Pediatric Use:

Safety and effectiveness in pediatric patients below the age of 12 years have not been established. Please refer to the CONTRAINDICATIONS and WARNINGS sections.

Geriatric Use:

Of the total number of subjects in clinical studies of 1.1% (w/v) sodium fluoride, 15 percent were 65 and over, while 1 percent were 75 and over. No overall differences in safety or effectiveness were observed between these subjects and younger subjects, and other reported clinical experience has not identified differences in responses between the elderly and younger patients, but greater sensitivity of some older individuals cannot be ruled out. This drug is known to be substantially excreted by the kidney, and the risk of toxic reactions to this drug may be greater in patients with impaired renal function. Because elderly patients are more likely to have decreased renal function, care
should be taken in dose selection, and it may be useful to monitor renal function.

ADVERSE REACTIONS:

Allergic reactions and other idiosyncrasies have been rarely reported. To report SUSPECTED ADVERSE REACTIONS, contact Rising Pharma Holdings, Inc. at 1-844-874-7464 or FDA at 1-800-FDA-1088 or www.fda.gov/medwatch.

OVERDOSAGE:

Accidental ingestion of large amounts of fluoride may result in acute burning in the mouth and sore tongue. Nausea, vomiting, and diarrhea may occur soon after ingestion (within 30 minutes) and are accompanied by salivation, hematemesis, and epigastric cramping abdominal pain. These symptoms may persist for 24 hours. If less than 5 mg fluoride/kg body weight (i.e., less than 2.3 mg fluoride/lb body weight) have been ingested, give calcium (e.g., milk) orally to relieve gastrointestinal symptoms and observe for a few hours. If more than 5 mg fluoride/kg body weight (i.e., more than 2.3 mg fluoride/lb body weight) have been ingested, induce vomiting, give orally soluble calcium (e.g., milk, 5% calcium gluconate or calcium lactate solution) and immediately seek medical assistance. For accidental ingestion of more than 15 mg fluoride/kg body weight (i.e., more than 6.9 mg fluoride/lb body weight), induce vomiting and admit immediately to a hospital facility.

A treatment dose (a thin ribbon) of Denta 5000 Plus Sensitive contains approximately 2.5 mg fluoride. A 3.4 FL OZ (100 mL) tube contains 575 mg fluoride.

DOSAGE AND ADMINISTRATION:

Follow these instructions unless otherwise instructed by your dental professional:

1. Adults and children 12 years of age or older: Apply at least a 1 inch strip of Denta 5000 Plus Sensitive onto a soft bristle toothbrush. Brush teeth thoroughly for at least 1 minute, expectorate, and rinse mouth thoroughly.
2. Use twice a day (morning and evening) or as recommended by a dentist or physician. Make sure to brush all sensitive areas of the teeth. Children under 12 years of age: Consult a dentist or physician.

HOW SUPPLIED: | MILD MINT
3.4 FL OZ (100 mL) net wt. tube | NDC # 16571-823-10

STORAGE:

Store at Controlled Room Temperature, 68-77°F (20-25°C).

Rx only REFERENCES:

1. American Dental Association, Accepted Dental Therapeutics Ed. 40 (Chicago, 1984): 405-407.
2. H.R. Englander et al., JADA 75 (1967): 638-644. 3. H.R. Englander et al, JADA 78 (1969): 783-787. 4. H.R. Englander et al., JADA 83 (1971):354-358.

Distributed by:

Rising Pharma Holdings, Inc.

East Brunswick, NJ 08816

Manufactured by:

Lyne Laboratories, Inc.

Brockton, MA 02301

Issued: 09/23

PRINCIPAL DISPLAY PANEL - 100 mL Container Label

Rising Pharma Holdings, Inc. NDC 16571-823-10

Denta 5000 Plus Sensitive

1.1% Sodium Fluoride, 5% Potassium Nitrate

Prescription Strength Toothpaste For Sensitive Teeth

Mild Mint

3.4 fl. OZ. (100 mL) Rx only